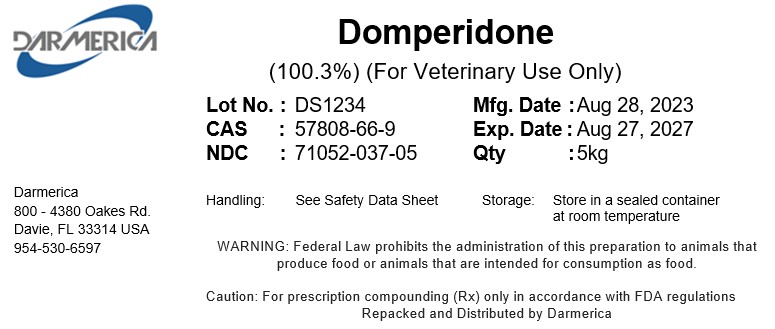 DRUG LABEL: Domperidone
NDC: 71052-037 | Form: POWDER
Manufacturer: DARMERICA, LLC
Category: other | Type: BULK INGREDIENT - ANIMAL DRUG
Date: 20260107

ACTIVE INGREDIENTS: Domperidone 1 kg/1 kg

Domperidone